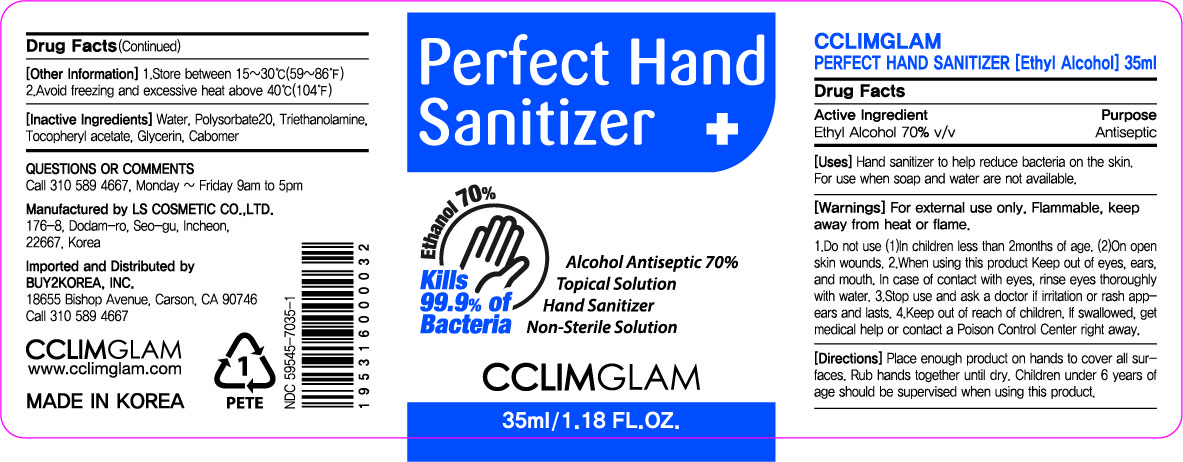 DRUG LABEL: CCLIMGLAM Perfect Hand Sanitizer
NDC: 59545-7035 | Form: GEL
Manufacturer: LS COSMETIC CO.,LTD.
Category: otc | Type: HUMAN OTC DRUG LABEL
Date: 20200515

ACTIVE INGREDIENTS: ALCOHOL 24.5 mL/35 mL
INACTIVE INGREDIENTS: ALPHA-TOCOPHEROL ACETATE; GLYCERIN; CARBOMER HOMOPOLYMER, UNSPECIFIED TYPE; WATER; TROLAMINE; POLYSORBATE 20

HANBAEG PRODUCT
CCLIMGLAM Perfect Hand Sanitizer (35 mL) : 59545-7035